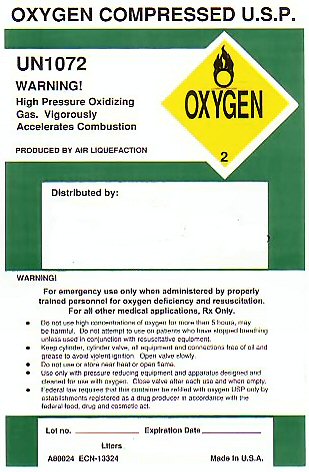 DRUG LABEL: OXYGEN
NDC: 45782-0000 | Form: GAS
Manufacturer: Mountain Valley Home Medical Equipment, Inc
Category: prescription | Type: HUMAN PRESCRIPTION DRUG LABEL
Date: 20100101

ACTIVE INGREDIENTS: OXYGEN 99 L/100 L

OXYGEN COMPRESSED LABEL

OXYGEN COMPRESSED USP UN1072 OXYGEN-2 WARNING HIGH PRESSURE OXIDIZING GAS. VIGOROUSLY ACCELERATES COMBUSTION. PRODUCED BY AIR LIQUEFACTION. WARNING: FOR EMERGENCY USE ONLY WHEN ADMINISTERED BY PROPERLY TRAINED PERSONNEL FOR OXYGEN DEFICIENCY AND RESUSCITATION. FOR ALL OTHER MEDICAL APPLICATIONS Rx ONLY. DO NOT USE HIGH CONCENTRATIONS OF OXYGEN FOR MORE THAT 5 HOURS, MAY BE HARMFUL. DO NOT ATTEMPT TO USE ON PATIENTS WHO HAVE STOPPED BREATHING UNLESS USED IN CONJUNCTION WITH RESUSCITATIVE EQUIPMENT. KEEP CYLINDER, CYLINDER VALVE, ALL EQUIPMENT AND CONNECTIONS FREE OF OIL AND GREASE TO AVOID VIOLENT IGNITION. OPEN VALVE SLOWLY. DO NOT USE OR STORE NEAR HEAT OR OPEN FLAME. USE ONLY WITH PRESSURE REDUCING EQUIPMENT AND APPARATUS DESIGNED AND CLEANED FOR USE WITH OXYGEN. CLOSE VALVE AFTER EACH USE AND WHEN EMPTY. FEDERAL LAW REQUIRES THIS CONTAINER BE REFILLED WITH OXYGEN USP ONLY BY ESTABLISHMENTS REGISTERED AS A DRUG PRODUCER IN ACCORDANCE WITH THE FEDERAL FOOD DRUG AND COSMETIC ACT.

LOT NUMBER__________ EXPIRATION DATE________________ LITERS________________ A80024 ECN-13324 MADE IN USA